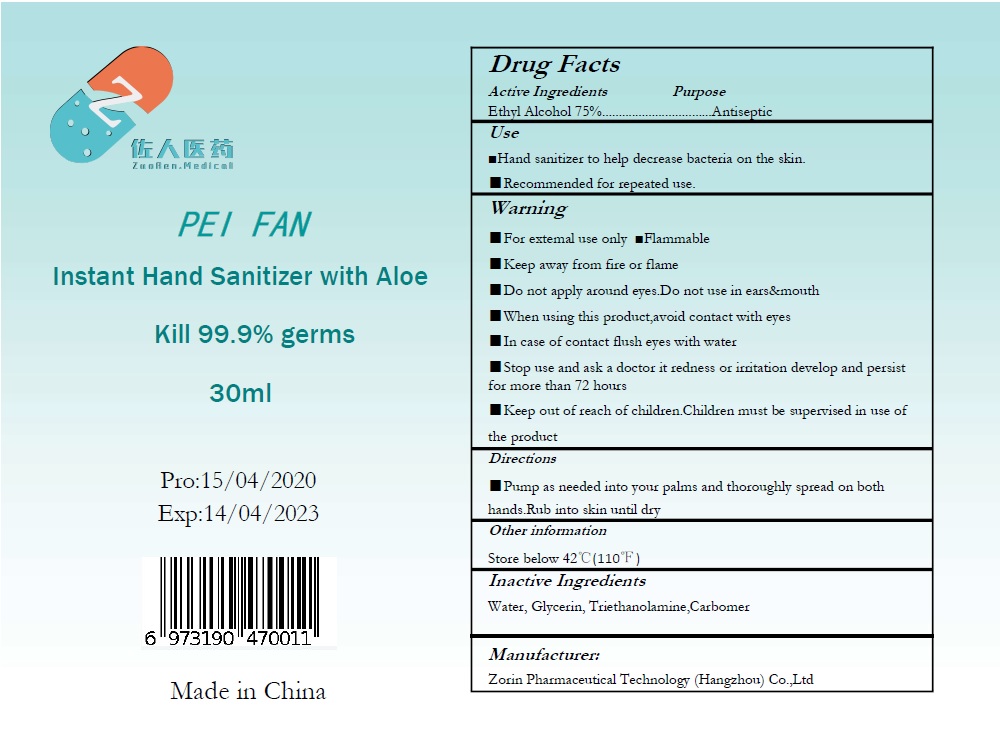 DRUG LABEL: PEI FAN Instant Sanitizer with Aloe
NDC: 75183-006 | Form: GEL
Manufacturer: Zorin Pharmaceutical Technology (Hangzhou) Co Ltd.
Category: otc | Type: HUMAN OTC DRUG LABEL
Date: 20200602

ACTIVE INGREDIENTS: ALCOHOL 75 mL/100 mL
INACTIVE INGREDIENTS: WATER; GLYCERIN; PROPYLENE GLYCOL; TROLAMINE; ALOE VERA LEAF

Active ingredient

Ethyl Alcohol 75%

Purpose

Antiseptic

Use

- Hand sanitizer to help decrease bacteria & virus on the skin
- Recommended for repeated use.

Warnings

For external use only.

Flammable,

Keep away from fire or flame

Do not apply around eyes, do not use in ears and mouth.

When using this product

avoid contact with eyes. In case of contact, flush eyes with water.

Stop use and ask a doctor if

redness or irritation develop and persist for more than 72 hours

KEEP OUT OF REACH OF CHILDREN

Children must be supervised in use of this product.

Directions

Pump as needed into your palms and thoroughly spread on both hands. Rub into skin until dry.

Inactive ingredients

Water, Triethanolamine, glycerin, Carbomer

Other information

Store below 42℃（110℉）